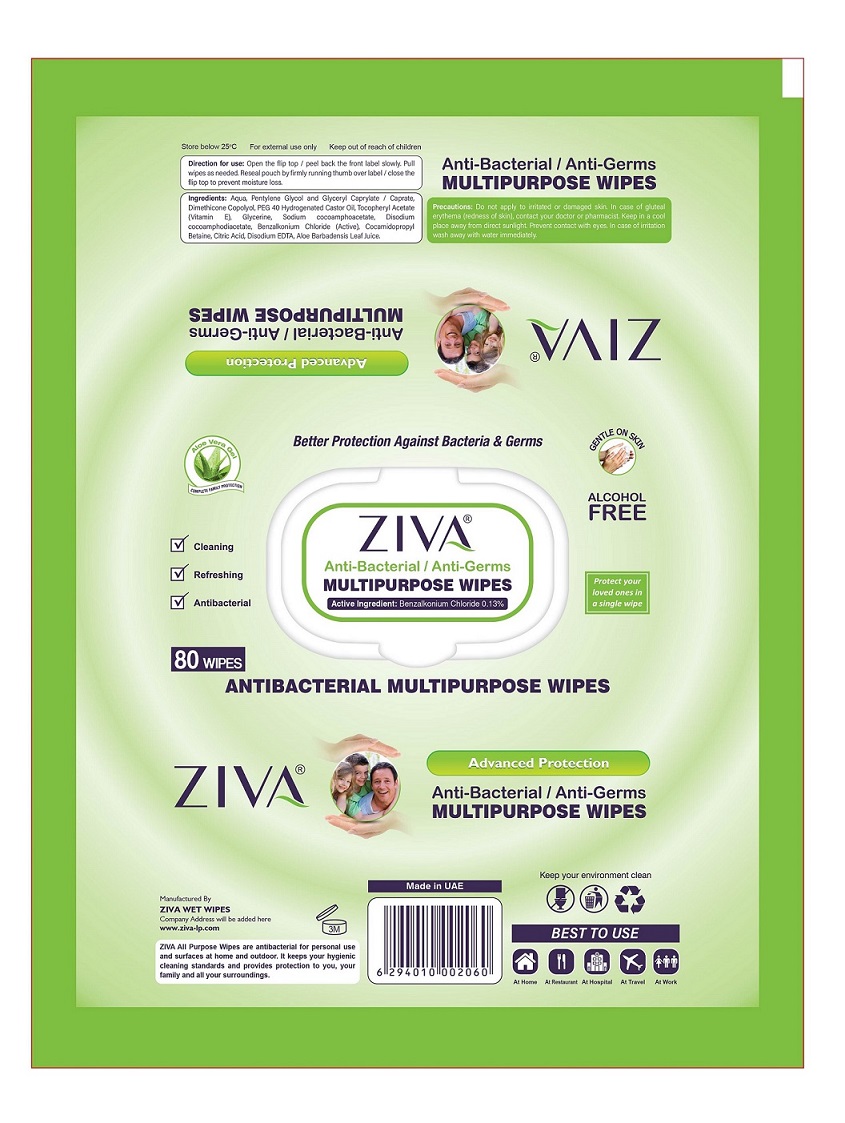 DRUG LABEL: ZIVA ANTIBACTERIAL MULTIPURPOSE WIPES
NDC: 81450-002 | Form: CLOTH
Manufacturer: Ziva Wetwipes FZCo
Category: otc | Type: HUMAN OTC DRUG LABEL
Date: 20231005

ACTIVE INGREDIENTS: BENZALKONIUM CHLORIDE 0.13 g/100 mL
INACTIVE INGREDIENTS: .ALPHA.-TOCOPHEROL ACETATE; PENTYLENE GLYCOL; GLYCERYL CAPRYLATE/CAPRATE; PEG/PPG-18/18 DIMETHICONE; SODIUM COCOAMPHOACETATE; COCAMIDOPROPYL BETAINE; WATER; HYDROGENATED CASTOR OIL; CITRIC ACID MONOHYDRATE; EDETATE DISODIUM; ALOE VERA LEAF; GLYCERIN; DISODIUM COCOAMPHODIACETATE

Drug Facts

Active Ingredient

Benzalkonium Chloride 0.13%

Direction of use:

Open the flip top / peel back the front label slowly. Pull wipes as needed. Reseal pouch by firmly running thumb over label / close the flip top to prevent moisture loss.

Precautions:

Do not apply to irritated or damaged skin. In case of gluteal erythema (redness of skin), contact your doctor or pharmacist. Keep in a cool place away from direct sunlight. Prevent contact with eyes. In case of irritation wash away with water immediately.

Ingredients:

Aqua, Pentylene Glycol and Glyceryl Caprylate / Caprate, Dimethicone copolyol, PEG 40 Hydrogenated Castor Oil, Tocopheryl Acetate (Vitamin E), Glycerine, Sodium cocoamphodiacetate, Cocamidopropyl Betaine, Citric Acid, Disodium EDTA, Aloe Barbadensis Leaf Juice.